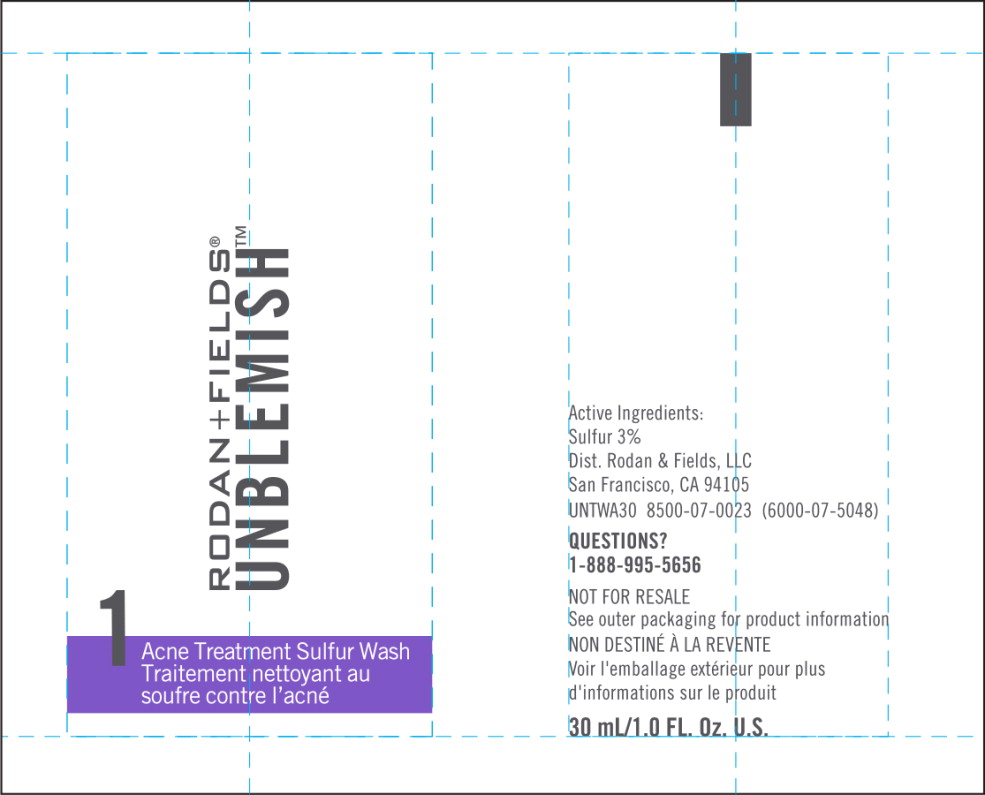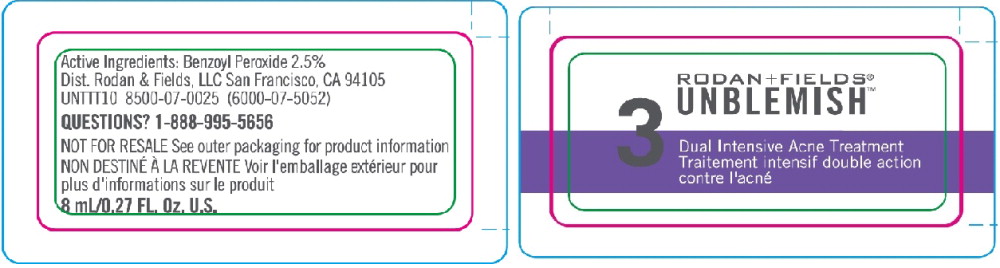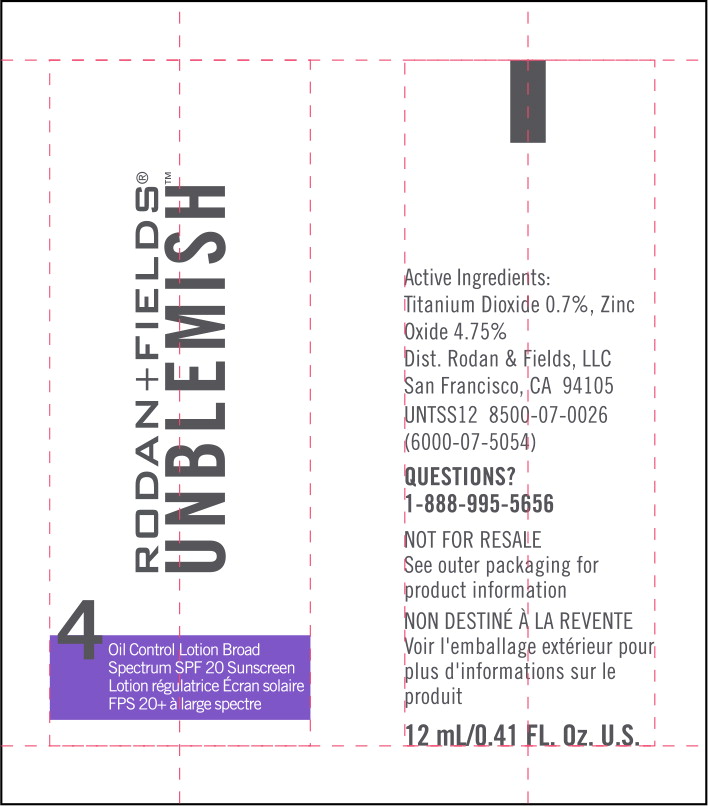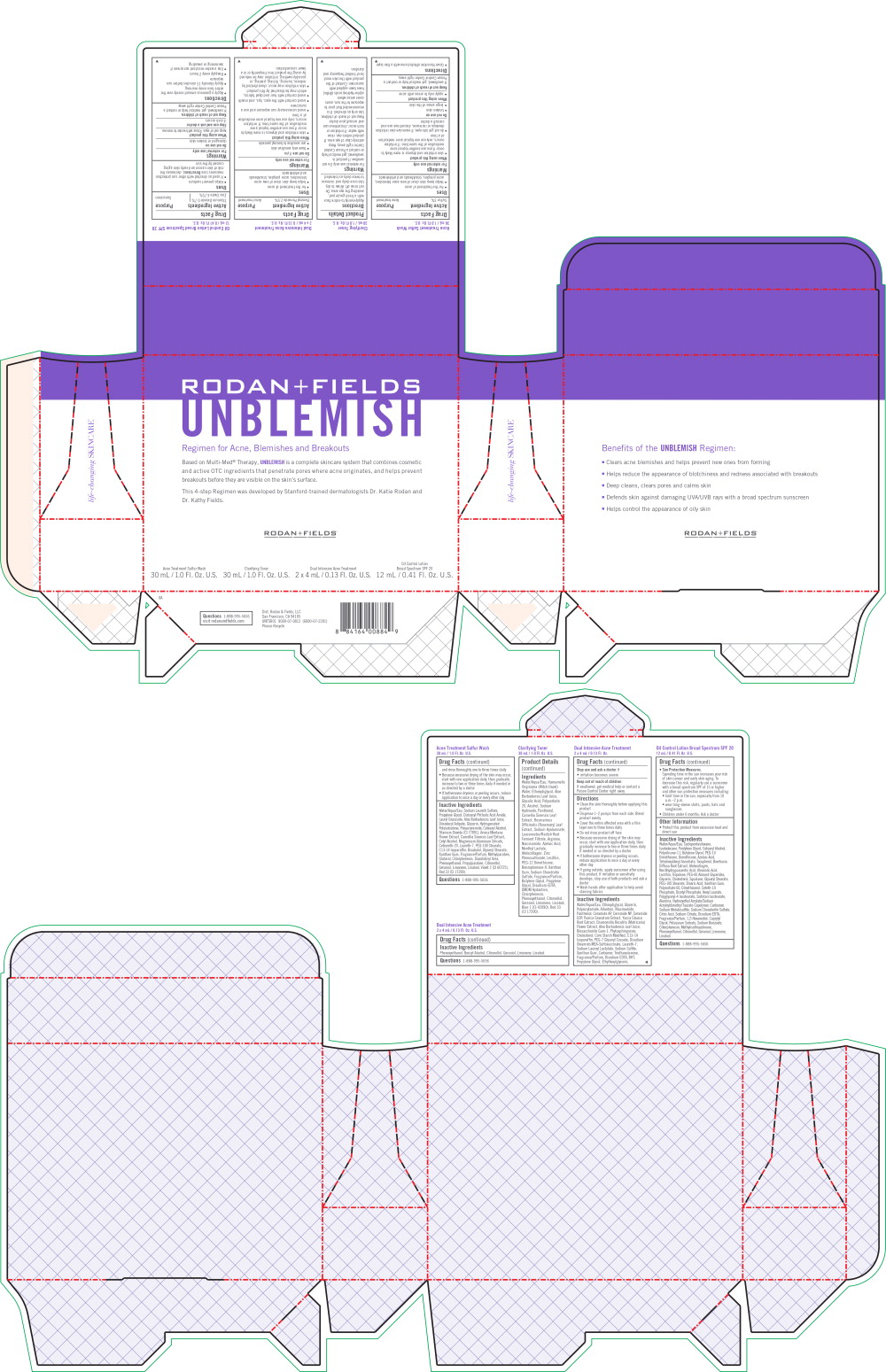 DRUG LABEL: UNBLEMISH Regimen for Acne, Blemishes and Breakouts Travel Size
NDC: 14222-2025 | Form: KIT | Route: TOPICAL
Manufacturer: Rodan & Fields, LLC. 

Category: otc | Type: HUMAN OTC DRUG LABEL
Date: 20170724

ACTIVE INGREDIENTS: Sulfur 3.0 g/100 mL; Benzoyl Peroxide 2.5 g/100 mL; Titanium Dioxide 0.7 g/100 mL; Zinc Oxide 4.75 g/100 mL
INACTIVE INGREDIENTS: Water; Sodium Laureth Sulfate; Propylene Glycol; Distearyl Phthalamic Acid; Lauryl Glucoside; Aloe Vera Leaf; Diisodecyl Adipate; Glycerin; Hydrogenated Polybutene (1300 MW); Polyacrylamide (1500 MW); Cetostearyl Alcohol; Titanium Dioxide; Arnica Montana Flower; Green Tea Leaf; Cetyl Alcohol; Magnesium Aluminum Silicate; Polyoxyl 20 Cetostearyl Ether; Laureth-7; PEG-100 Stearate; C13-14 Isoparaffin; Levomenol; Glyceryl Monostearate; Xanthan Gum; Methylparaben; Glutaral; Chlorphenesin; Diazolidinyl Urea; Phenoxyethanol; Propylparaben; .Beta.-Citronellol, (R)-; Geraniol; Limonene, (+)-; Linalool, (+/-)-; D&C Violet No. 2; D&C Red No. 33; Water; Diethylene Glycol Monoethyl Ether; Glycerin; Polyacrylamide (1500 MW); Allantoin; Niacinamide; Panthenol; Ceramide AP; Ceramide NP; Ceramide 1; Punica Granatum Root Bark; Yucca Glauca Root; Chamomile; Aloe Vera Leaf; Biosaccharide Gum-1; Phytosphingosine; Cholesterol; Modified Corn Starch (1-Octenyl Succinic Anhydride); C13-14 Isoparaffin; PEG-7 Glyceryl Cocoate; Disodium Oleamido MEA-Sulfosuccinate; Laureth-7; Sodium Lauroyl Lactylate; Sodium Sulfite; Xanthan Gum; Carboxypolymethylene; Trolamine; Edetate Disodium Anhydrous; Butylated Hydroxytoluene; Propylene Glycol; Ethylhexylglycerin; Phenoxyethanol; Benzyl Alcohol; .Beta.-Citronellol, (R)-; Geraniol; Limonene, (+)-; Linalool, (+/-)-; Water; Cyclomethicone 5; Isododecane; Pentylene Glycol; Cetostearyl Alcohol; Dimethicone/Vinyl Dimethicone Crosspolymer (Soft Particle); Butylene Glycol; PEG-10 Dimethicone (600 CST); Dimethicone; Azelaic Acid; Tetrahexyldecyl Ascorbate; Tocopherol; Boerhavia Diffusa Root; Marine Collagen, Soluble; Nordihydroguaiaretic Acid, (+/-)-; Oleanolic Acid; Lecithin, Soybean; Tropolone; PEG-60 Almond Glycerides; Glycerin; Cholesterol; Squalane; Glyceryl Monostearate; PEG-100 Stearate; Stearic Acid; Xanthan Gum; Polysorbate 60; Dimethiconol (70 CST); Ceteth-10 Phosphate; Dihexadecyl Phosphate; Hexyl Laurate; Polyglyceryl-4 Isostearate; Sorbitan Isostearate; Aluminum Oxide; Hydroxyethyl Acrylate/Sodium Acryloyldimethyl Taurate Copolymer (100000 MPA.S At 1.5%); Carboxypolymethylene; Sodium Metabisulfite; Chondroitin Sulfate Sodium (Bovine); Citric Acid Monohydrate; Sodium Citrate; Edetate Disodium Anhydrous; 1,2-Hexanediol; Caprylyl Glycol; Potassium Sorbate; Sodium Benzoate; Chlorphenesin; Methylisothiazolinone; Phenoxyethanol; .Beta.-Citronellol, (R)-; Geraniol; Limonene, (+)-; Linalool, (+/-)-

Acne Treatment Sulfur Wash

30 mL / 1.0 Fl. Oz. U.S.

Drug Facts

Active Ingredient

Sulfur 3%

Purpose

Acne treatment

Uses

- For the treatment of acne
- Helps keep skin clear of new acne blemishes, acne pimples, blackheads and whiteheads

Warnings

For external use only

When using this product

- skin irritation and dryness is more likely to occur if you use another topical acne medication at the same time. If irritation occurs, only use one topical acne medication at a time
- do not get into eyes. If excessive skin irritation develops or increases, discontinue use and consult a doctor

Do not use on

- broken skin
- large areas of the skin

When using this product

- apply only to areas with acne

Keep out of reach of children.

If swallowed, get medical help or contact a Poison Control Center right away.

Directions

- Cover the entire affected area with a thin layer and rinse thoroughly one to three times daily
- Because excessive drying of the skin may occur, start with one application daily, then gradually increase to two or three times daily if needed or as directed by a doctor
- If bothersome dryness or peeling occurs, reduce application to once a day or every other day

Inactive Ingredients

Water/Aqua/Eau, Sodium Laureth Sulfate, Propylene Glycol, Distearyl Phthalic Acid Amide, Lauryl Glucoside, Aloe Barbadensis Leaf Juice, Diisodecyl Adipate, Glycerin, Hydrogenated Polyisobutene, Polyacrylamide, Cetearyl Alcohol, Titanium Dioxide (CI 77891), Arnica Montana Flower Extract, Camellia Sinensis Leaf Extract, Cetyl Alcohol, Magnesium Aluminum Silicate, Ceteareth-20, Laureth-7, PEG-100 Stearate, C13-14 Isoparaffin, Bisabolol, Glyceryl Stearate, Xanthan Gum, Fragrance/Parfum, Methylparaben, Glutaral, Chlorphenesin, Diazolidinyl Urea, Phenoxyethanol, Propylparaben, Citronellol, Geraniol, Limonene, Linalool, Violet 2 (CI 60725), Red 33 (CI 17200).

Questions 1-888-995-5656

Clarifying Toner

30 mL / 1.0 Fl. Oz. U.S.

Product Details

Directions

Apply evenly to entire face with a fresh gauze pad, avoiding the eye area. Do not rinse off. Allow to dry. Use once daily and increase to twice daily as tolerated.

Warnings

For external use only. Do not swallow. If product is swallowed, get medical help or contact a Poison Control Centre right away. Keep entirely clear of eye area. If product enters eye, rinse with water. If irritation or rash occur, discontinue use and consult your doctor. Keep out of reach of children. Use only as directed. It is recommended that prior to exposure to the sun, users cover areas where alpha-hydroxy acids (AHAs) have been applied with sunscreen. Contact of the product with the skin must be of limited frequency and duration.

Ingredients

Water/Aqua/Eau, Hamamelis Virginiana (Witch Hazel) Water, Ethoxydiglycol, Aloe Barbadensis Leaf Juice, Glycolic Acid, Polysorbate 20, Alcohol, Sodium Hydroxide, Panthenol, Camellia Sinensis Leaf Extract, Rosmarinus Officinalis (Rosemary) Leaf Extract, Sodium Hyaluronate, Leuconostoc/Radish Root Ferment Filtrate, Arginine, Niacinamide, Azelaic Acid, Menthyl Lactate, Atelocollagen, Zinc Phenosulfonate, Lecithin, PEG-12 Dimethicone, Benzophenone-9, Xanthan Gum, Sodium Chondrotin Sulfate, Fragrance/Parfum, Butylene Glycol, Propylene Glycol, Disodium EDTA, DMDM Hydantoin, Chlorphenesin, Phenoxyethanol, Citronellol, Geraniol, Limonene, Linalool, Blue 1 (CI 42090), Red 33 (CI 17200).

Dual Intensive Acne Treatment

2 x 4 mL / 0.13 Fl. Oz. U.S.

Drug Facts

Active Ingredient

Benzoyl Peroxide 2.5%

Purpose

Acne treatment

Uses

- for the treatment of acne
- helps keep skin clear of new acne blemishes, acne pimples, blackheads and whiteheads

Warnings

For external use only

Do not use if you

- have very sensitive skin
- are sensitive to benzoyl peroxide

When using this product

- skin irritation and dryness is more likely to occur if you use another topical acne medication at the same time. If irritation occurs, only use one topical acne medication at a time
- avoid unnecessary sun exposure and use a sunscreen
- avoid contact with the eyes, lips, and mouth
- avoid contact with hair and dyed fabrics, which may be bleached by this product
- skin irritation may occur, characterized by redness, burning, itching, peeling, or possibly swelling. Irritation may be reduced by using the product less frequently or in a lower concentration.

Stop use and ask a doctor if

- irritation becomes severe

Keep out of reach of children

If swallowed, get medical help or contact a Poison Control Center right away

Directions

- Clean the skin thoroughly before applying this product
- Dispense 1–2 pumps from each side. Blend product evenly
- Cover the entire affected area with a thin layer one to three times daily
- Do not rinse product off face
- Because excessive drying of the skin may occur, start with one application daily, then gradually increase to two or three times daily if needed or as directed by a doctor
- If bothersome dryness or peeling occurs, reduce application to once a day or every other day
- If going outside, apply sunscreen after using this product. If irritation or sensitivity develops, stop use of both products and ask a doctor
- Wash hands after application to help avoid staining fabrics

Inactive Ingredients

Water/Aqua/Eau, Ethoxydiglycol, Glycerin, Polyacrylamide, Allantoin, Niacinamide, Panthenol, Ceramide AP, Ceramide NP, Ceramide EOP, Punica Granatum Extract, Yucca Glauca Root Extract, Chamomilla Recutita (Matricaria) Flower Extract, Aloe Barbadensis Leaf Juice, Biosaccharide Gum-1, Phytosphingosine, Cholesterol, Corn Starch Modified, C13-14 Isoparaffin, PEG-7 Glyceryl Cocoate, Disodium Oleamido MEA-Sulfosuccinate, Laureth-7, Sodium Lauroyl Lactylate, Sodium Sulfite, Xanthan Gum, Carbomer, Triethanolamine, Fragrance/Parfum, Disodium EDTA, BHT, Propylene Glycol, Ethylhexylglycerin, Phenoxyethanol, Benzyl Alcohol, Citronellol, Geraniol, Limonene, Linalool.

Questions 1-888-995-5656

Oil Control Lotion Broad Spectrum SPF 20

12 mL / 0.41 Fl. Oz. U.S.

Drug Facts

Active Ingredients

Titanium Dioxide 0.7%

Zinc Oxide 4.75%

Purpose

Sunscreen

Uses

- Helps prevent sunburn
- If used as directed with other sun protection measures (see Directions), decreases the risk of skin cancer and early skin aging caused by the sun

Warnings

For external use only

Do not use on

damaged or broken skin

When using this product

keep out of eyes. Rinse with water to remove.

Stop use and ask a doctor

if rash occurs

Keep out of reach of children.

If swallowed, get medical help or contact a Poison Control Center right away.

Directions

- Apply a generous amount evenly over the entire face every morning
- Apply liberally 15 minutes before sun exposure
- Reapply every 2 hours
- Use a water-resistant sunscreen if swimming or sweating
- Sun Protection Measures.
  Spending time in the sun increases your risk of skin cancer and early skin aging. To decrease this risk, regularly use a sunscreen with a broad spectrum SPF of 15 or higher and other sun protection measures including:
  - limit time in the sun, especially from 10 a.m.–2 p.m.
  - wear long-sleeve shirts, pants, hats and sunglasses
- Children under 6 months: Ask a doctor

Other Information

- Protect this product from excessive heat and direct sun

Inactive Ingredients

Water/Aqua/Eau, Cyclopentasiloxane, Isododecane, Pentylene Glycol, Cetearyl Alcohol, Polysilicone-11, Butylene Glycol, PEG-10 Dimethicone, Dimethicone, Azelaic Acid, Tetrahexyldecyl Ascorbate, Tocopherol, Boerhavia Diffusa Root Extract, Atelocollagen, Nordihydroguaiaretic Acid, Oleanolic Acid, Lecithin, Tropolone, PEG-60 Almond Glycerides, Glycerin, Cholesterol, Squalane, Glyceryl Stearate, PEG-100 Stearate, Stearic Acid, Xanthan Gum, Polysorbate 60, Dimethiconol, Ceteth-10 Phosphate, Dicetyl Phosphate, Hexyl Laurate, Polyglyceryl-4 Isostearate, Sorbitan Isostearate, Alumina, Hydroxyethyl Acrylate/Sodium Acryloyldimethyl Taurate Copolymer, Carbomer, Sodium Metabisulfite, Sodium Chondroitin Sulfate, Citric Acid, Sodium Citrate, Disodium EDTA, Fragrance/Parfum, 1,2-Hexanediol, Caprylyl Glycol, Potassium Sorbate, Sodium Benzoate, Chlorphenesin, Methylisothiazolinone, Phenoxyethanol, Citronellol, Geraniol, Limonene, Linalool.

Questions 1-888-995-5656

Principal Display Panel - Rodan Fields Unblemish Acne Treatment Sulfur Wash Label

RODAN + FIELDS®
UNBLEMISH™

1 Acne Treatment Sulfur Was

Traitement nettoyant au
soufre contre l'acné

Principal display Panel - Rodan Fields Unblemish Dual Intensive Acne Treatment Label

RODAN + FIELDS®
UNBLEMISH™

3 Dual Intensive Acne Treatment

Traitement intensif double action
contre l'acné

Principal display Panel - Rodan Fields Unblemish Oil Control Lotion Label

RODAN + FIELDS®
UNBLEMISH™

4 Oil Control Lotion Broad Spectrum SPF 20 Sunscreen

Lotion régulatrice Écran solaire
FPS 20+ à large spectre

Principal display Panel - Rodan Fields Unblemish Kit Label

RODAN + FIELDS®
UNBLEMISH

Regiment for Acne, Blemishes and Breakouts

Based on Multi-Med® Therapy, UNBLEMISH is a complete skincare system that combines cosmetic
and active OTC ingredients that penetrate pores where acne originates, and helps prevent
breakouts before they are visible on the skin's surface.

This 4-product Regimen was developed by Stanford-trained dermatologists Dr. Katie Rodan and
Dr. Kathy Fields.

RODAN + FIELDS®

Acne Treatment Sulfur Wash

30 mL/ 1.0 Fl.Oz. U.S.

Clarifying Toner

30 mL/ 1.0 Fl.Oz. U.S.

Dual Intensive Acne Treatment

2 x 4 mL/0.13 Fl.Oz. U.S.

Oil Control Lotion
Broad Spectrum SPF 20

12 mL/0.41 Fl.Oz. U.S.